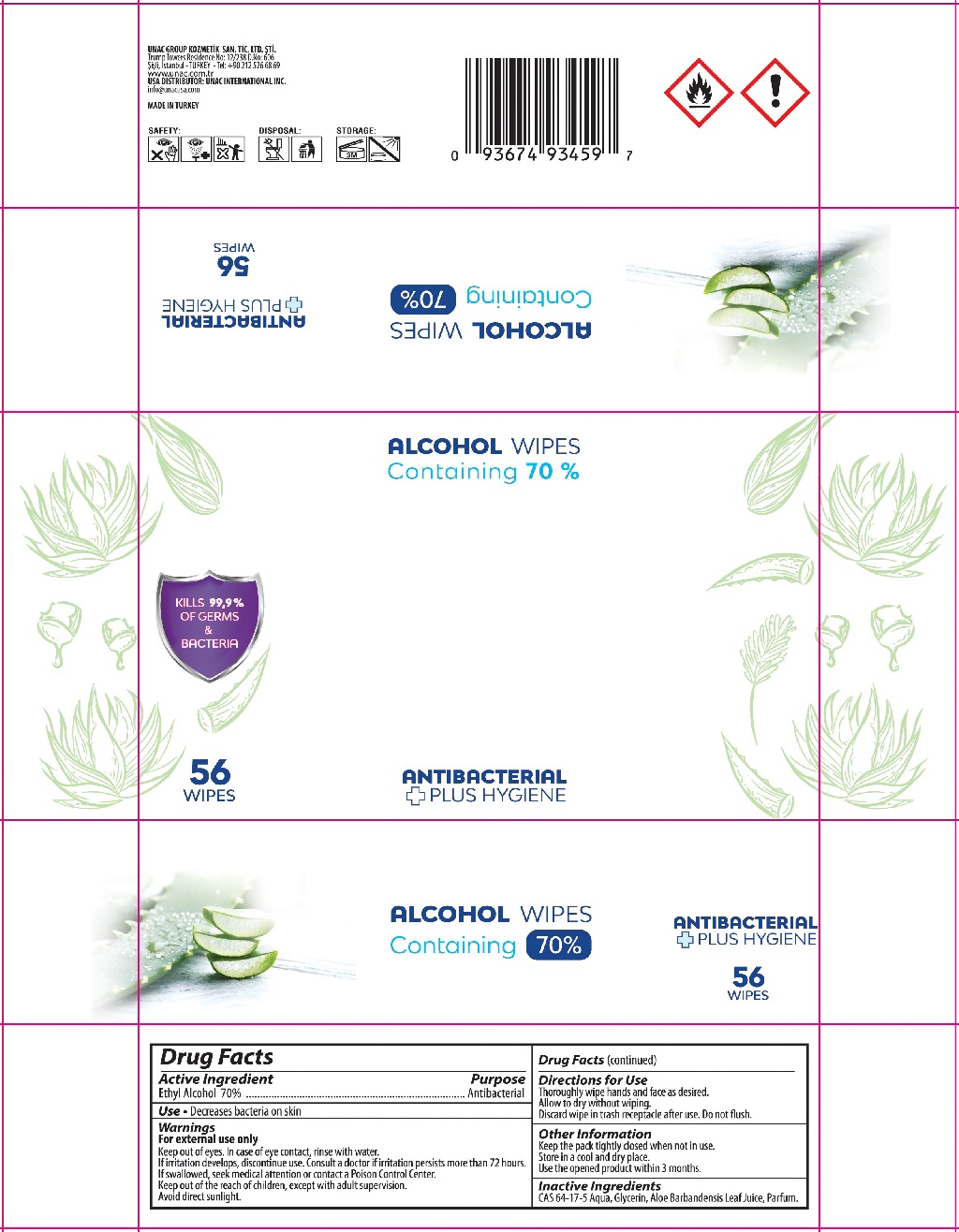 DRUG LABEL: BREEZE
NDC: 74955-027 | Form: CLOTH
Manufacturer: COSMOLIVE KOZMETIK SANAYI VE TICARET ANONIM SIRKETI
Category: otc | Type: HUMAN OTC DRUG LABEL
Date: 20200903

ACTIVE INGREDIENTS: ALCOHOL 70 g/100 g
INACTIVE INGREDIENTS: WATER; GLYCERIN; ALOE VERA LEAF

ALCOHOL WIPES ANTIBACTERIAL PLUS HYGIENE

Active Ingredient

Ethyl Alcohol 70%

Purpose

Antibacterial

INDICATIONS AND USAGE

Use • Decreases bacteria on skin

Warnings

For external use only

Keep out of eyes. In case of eye contact, rinse with water.

If irritation develops, discontinue use. Consult a doctor if irritation persists more than 72 hours.

If swallowed, seek medical attention or contact a Poison Control Center.

Avoid direct sunlight.

KEEP OUT OF REACH OF CHILDREN

Keep out of the reach of children, except with adult supervision.

Directions for use

Thoroughly wipe hands and face as desired.

Allow to dry without wiping.

Discard wipe in trash receptacle after use. Do not flush.

Other Information

Keep the pack tightly closed when not in use.

Store in a cool and dry place.

Use the opened product within 3 months.

Inactive Ingredients

CAS 64-17-5 Aqua, Glycerin, Aloe Barbadensis Leaf Juice, Parfum.

KILLS 99,9% OF GERMS & BACTERIA

Containing 70%

UNAC GROUP KOZMETİK SAN. TİC. LTD. ŞTİ

Trump Towers Residence No: 12/238 D.No:606

Şişli, Istanbul- TURKEY - Tel: +90 212 526 68 69

www.unac.com.tr

USA DISTRIBUTOR: UNAC INTERNATIONAL INC.

info@unacusa.com

MADE IN TURKEY